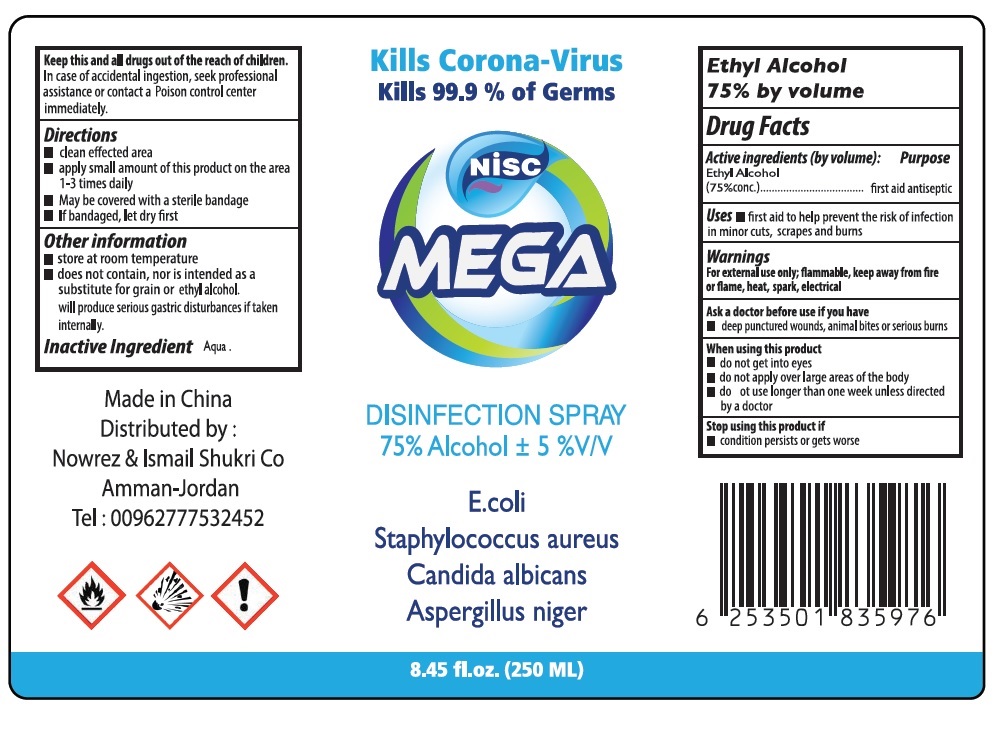 DRUG LABEL: NISC MEGA DISINFECTION
NDC: 75771-232 | Form: SPRAY
Manufacturer: NOWREZ & ISMAIL SHUKRI COMPANY
Category: otc | Type: HUMAN OTC DRUG LABEL
Date: 20200424

ACTIVE INGREDIENTS: ALCOHOL 75 mL/100 mL
INACTIVE INGREDIENTS: WATER

NISC MEGA DISINFECTION SPRAY

Ethyl Alcohol 75% by volume

Drug Facts

Active ingredients (by volume):

Ethyl Alcohol (75% conc.)

Purpose

first aid antiseptic

Uses

• first aid to help prevent the risk of infection in minor cuts, scrapes and burns

Warnings

For external use only; flammable, keep away from fire or flame, heat, spark, electrical

Ask a doctor before use if you have

• deep punctured wounds, animal bites or serious burns

Whe using this product

•do not get into eyes

•do not apply over large areas of the body

•do not use longer than one week unless directed by a doctor

Stop using this product if

•condition persists or gets worse

Keep this and all drugs out of the reach of children.

In case of accidental ingestion, seek professional assistance or contact a Poison Control Center immediately.

Directions

• clean effected area

• apply small amount of this product on the area 1-3 times daily

• May be covered with a sterile bandage

• If bandaged, let dry first

Other information

• store at room temperature

• does not contain, nor is intended as a substitute for grain or ethyl alcohol.

will produce serious gastric disturbances if taken internally.

Inactive Ingredient

Aqua.

Kills Corona-Virus

Kills 99.9% of Germs

75% Alcohol ± 5 %V/V

E.coli

Staphylococcus aureus

Candida albicans

Aspergillus niger

Made in China

Distributed by :

Nowrez & Ismail Shukri Co

Amman- Jordan

Tel : 00962777532452